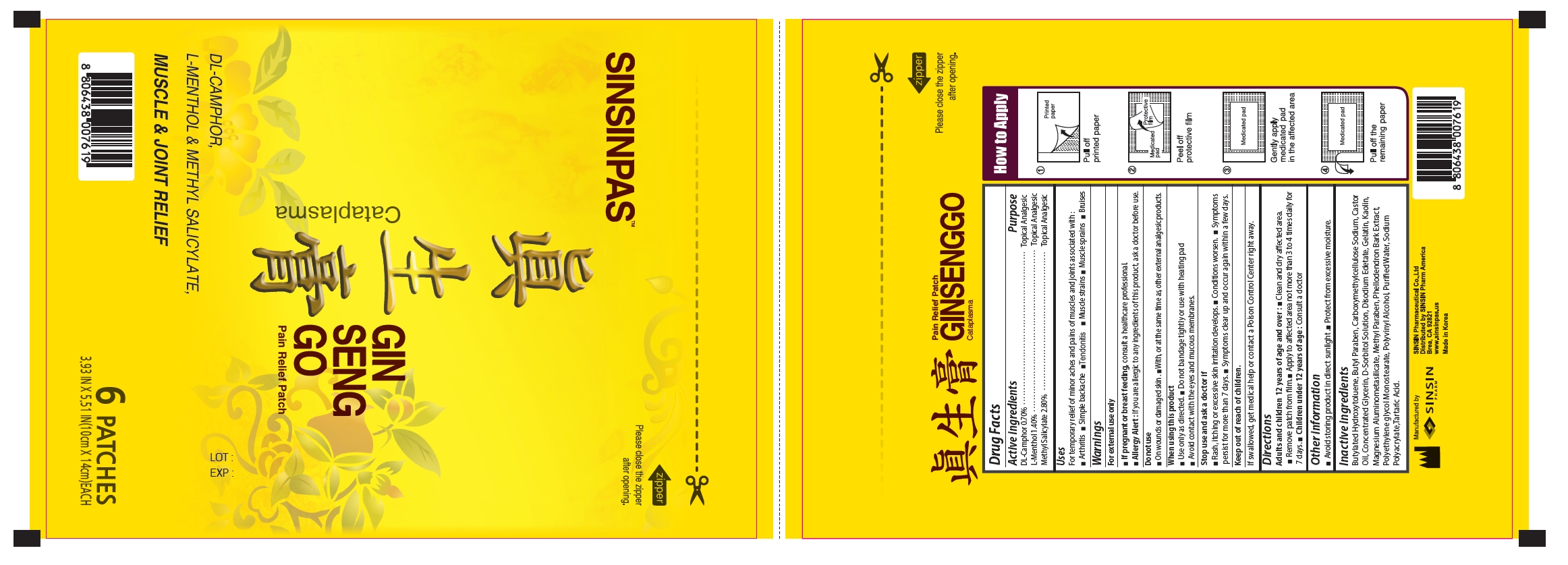 DRUG LABEL: GINSENGGO
NDC: 55264-005 | Form: PATCH
Manufacturer: Sinsin Pharmaceutical Co., Ltd.
Category: otc | Type: HUMAN OTC DRUG LABEL
Date: 20201113

ACTIVE INGREDIENTS: CAMPHOR (SYNTHETIC) 0.7 mg/1 1; LEVOMENTHOL 1.4 mg/1 1; METHYL SALICYLATE 2.8 mg/1 1
INACTIVE INGREDIENTS: BUTYLATED HYDROXYTOLUENE; BUTYLPARABEN; CARBOXYMETHYLCELLULOSE SODIUM; CASTOR OIL; GLYCERIN; SORBITOL; EDETATE DISODIUM; GELATIN; KAOLIN; SILODRATE; METHYLPARABEN; PHELLODENDRON AMURENSE BARK; PEG-8 STEARATE; POLYVINYL ALCOHOL; WATER; SODIUM POLYACRYLATE (2500000 MW); TARTARIC ACID

Drug Facts

Active ingredients

DL-Camphor 0.70%

L-Menthol 1.40%

Methyl Salicylate 2.80%

Purpose

Topical Analgesic

Uses

for temporary relief of minor pain associated with:

- Arthritis
- Simple backache
- Tendonitis
- Muscle strains
- Muscle sprains
- Bruises

Warnings

For external use only.

- If pregnant or breast feeding, consult a healthcare professional.
- Allergy Alert: If you are allergic to any ingredients of this product, ask a doctor before use.

Do not use

- on wounds or damaged skin
- with, or at the same time as, other external analgesic products.

When using this product

- use only as directed
- do not bandage tightly or use with heating pad.
- avoid contact with the eyes and mucous membranes.

Stop use and ask a doctor if

- conditions worsens.
- symptoms persist more than 7 days or clear up and occur again within a few days.
- rash, itiching, or excessive irritation develops.

Keep out of reach of children.

If swallowed, get medical help or contact a Poison Control Center right away.

Directions

Adults and children 12 years of age and older

- clean and dry affected area
- remove patch from film.
- apply to affected area not more than 3 to 4 times daily for 7 days.

Children under 12 years of age consult a doctor

Reseal pouch containing used portion patched

Other information

- avoid storing product in direct sunlight
- protect product from excessive moisture

Inactive ingredients

Butylated Hydroxy Toluene, Butyl Paraben, Carboxymethylcellulose sodium, Castor Oil, Concentrated Glycerin, D-Sorbitol Solution, Disodium Edetate, Gelatin, Kaolin, Magnesium Aluminometasilicate, Methyl paraben, Phellodendron Bark Extract, Polyethylene glycol Monostearate, Polyvinyl Alcohol, Purified Water, Sodium Polyacrylate, Tartaric acid

How To Apply

1. Pull off printed paper

2. Peel off protective film

3. Gently apply medicated pad in the affected area

4. Pull off the remaining paper

Manufactured by:

SINSIN PHARM. CO., LTD.

http://www.sinsin.com tel: 82-31-776-1140~3

776-6, Wonsi-Dong, Danwon-Gu, Ansan City, Kyunggi-Do, Korea

Made in Korea